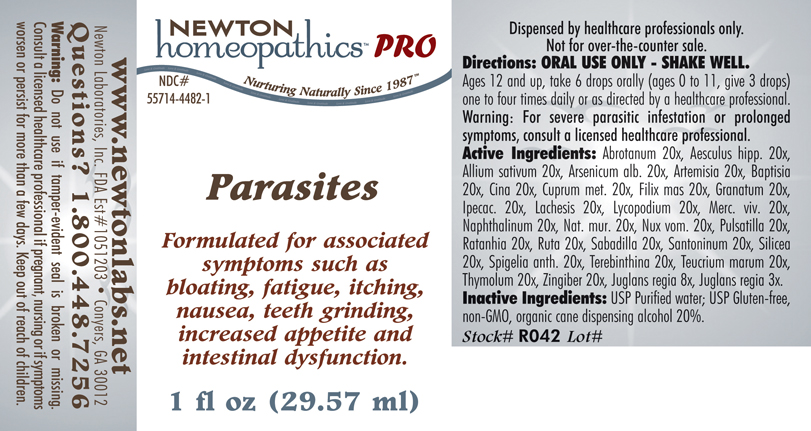 DRUG LABEL: Parasites 
NDC: 55714-4482 | Form: LIQUID
Manufacturer: Newton Laboratories, Inc.
Category: homeopathic | Type: HUMAN PRESCRIPTION DRUG LABEL
Date: 20110601

ACTIVE INGREDIENTS: Artemisia Abrotanum Flowering Top 20 [hp_X]/1 mL; Horse Chestnut 20 [hp_X]/1 mL; Garlic 20 [hp_X]/1 mL; Arsenic Trioxide 20 [hp_X]/1 mL; Baptisia Tinctoria Root 20 [hp_X]/1 mL; Artemisia Maritima Pre-flowering Top 20 [hp_X]/1 mL; Copper 20 [hp_X]/1 mL; Dryopteris Filix-mas Root 20 [hp_X]/1 mL; Punica Granatum Root Bark 20 [hp_X]/1 mL; Ipecac 20 [hp_X]/1 mL; Lachesis Muta Venom 20 [hp_X]/1 mL; Lycopodium Clavatum Spore 20 [hp_X]/1 mL; Mercury 20 [hp_X]/1 mL; Naphthalene 20 [hp_X]/1 mL; Sodium Chloride 20 [hp_X]/1 mL; Strychnos Nux-vomica Seed 20 [hp_X]/1 mL; Pulsatilla Vulgaris 20 [hp_X]/1 mL; Krameria Lappacea Root 20 [hp_X]/1 mL; Ruta Graveolens Flowering Top 20 [hp_X]/1 mL; Schoenocaulon Officinale Seed 20 [hp_X]/1 mL; Santonin 20 [hp_X]/1 mL; Silicon Dioxide 20 [hp_X]/1 mL; Spigelia Anthelmia 20 [hp_X]/1 mL; Turpentine Oil 20 [hp_X]/1 mL; Teucrium Marum 20 [hp_X]/1 mL; Thymol 20 [hp_X]/1 mL; Ginger 20 [hp_X]/1 mL; English Walnut 8 [hp_X]/1 mL
INACTIVE INGREDIENTS: Alcohol

Parasites

INDICATIONS & USAGE SECTION

Parasites Formulated for associated symptoms such as bloating, fatigue, itching, nausea, teeth grinding, increased appetite and intestinal dysfunction.

DOSAGE & ADMINISTRATION SECTION

Directions: ORAL USE ONLY - SHAKE WELL. Ages 12 and up, take 6 drops orally (ages 0 to 11, give 3 drops) one to four times daily or as directed by a healthcare professional. Warning: For severe parasitic infestation or prolonged symptoms, consult a licensed healthcare professional.

ACTIVE INGREDIENT SECTION

Abrotanum 20x, Aesculus hipp. 20x, Allium sativum 20x, Arsenicum alb. 20x, Artemisia 20x, Baptisia 20x, Cina 20x, Cuprum met. 20x, Filix mas 20x, Granatum 20x, Ipecac. 20x, Lachesis 20x, Lycopodium 20x, Merc. viv. 20x, Naphthalinum 20x, Nat. mur. 20x, Nux vom. 20x, Pulsatilla 20x, Ratanhia 20x, Ruta 20x, Sabadilla 20x, Santoninum 20x, Silicea 20x, Spigelia anth. 20x, Terebinthina 20x, Teucrium marum 20x, Thymolum 20x, Zingiber 20x, Juglans regia 8x, Juglans regia 3x.

PURPOSE SECTION

Formulated for associated symptoms such as bloating, fatigue, itching, nausea, teeth grinding, increased appetite and intestinal dysfunction.

INACTIVE INGREDIENT SECTION

Inactive Ingredients: USP Purified Water; USP Gluten-free, non-GMO, organic cane dispensing alcohol 20%.

QUESTIONS? SECTION

www.newtonlabs.net Newton Laboratories, Inc. FDA Est # 1051203 - Conyers, GA 30012
Questions? 1.800.448.7256

WARNINGS SECTION

Warning: Do not use if tamper - evident seal is broken or missing. Consult a licensed healthcare professional if pregnant, nursing or if symptoms worsen or persist for more than a few days. Keep out of reach of children.

PREGNANCY OR BREAST FEEDING SECTION

Consult a licensed healthcare professional if pregnant, nursing or if symptoms worsen or persist for more than a few days.

KEEP OUT OF REACH OF CHILDREN SECTION

Keep out of reach of children